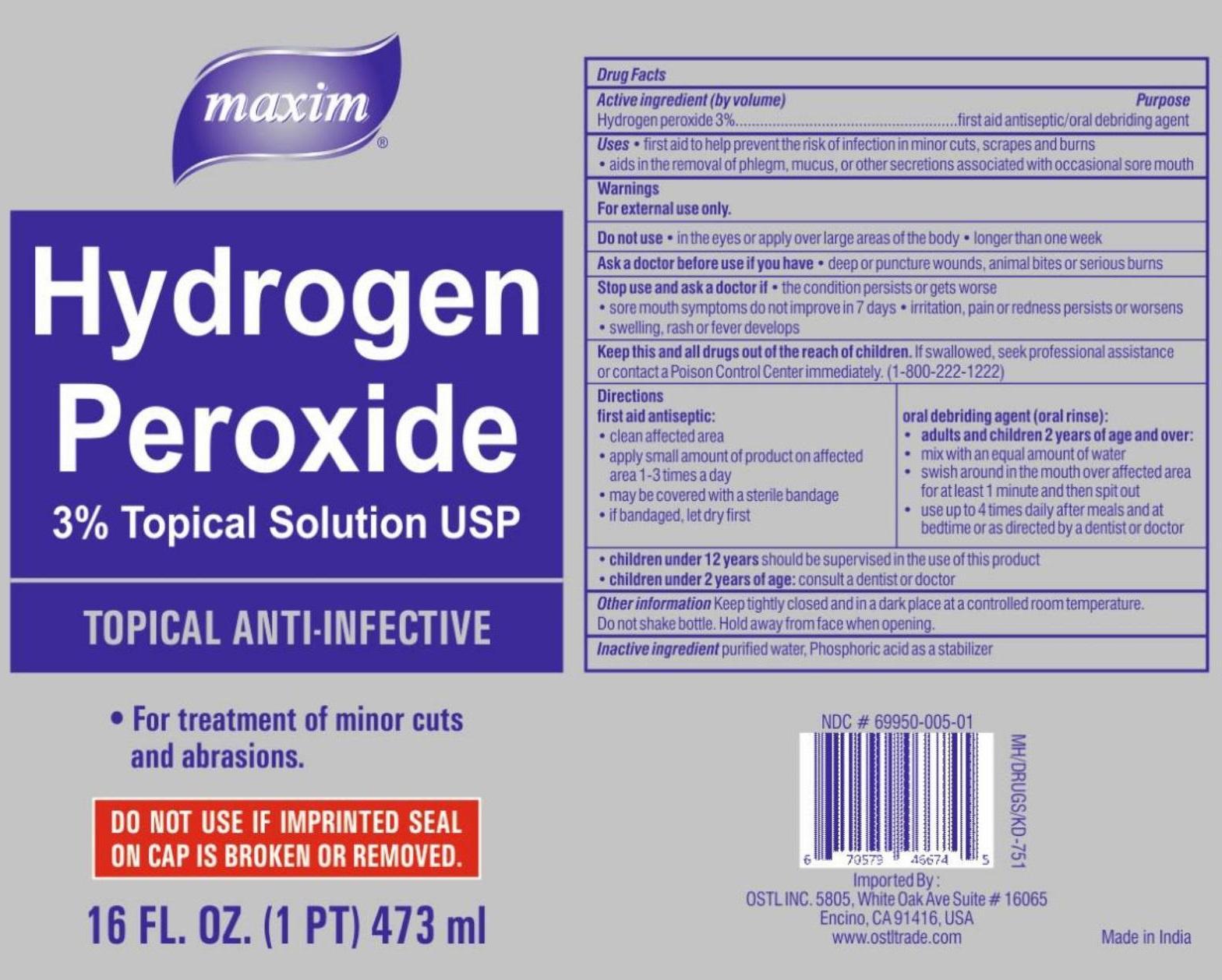 DRUG LABEL: maxim Hydrogen Peroxide
NDC: 69950-005 | Form: LIQUID
Manufacturer: Ostl, Inc.
Category: otc | Type: HUMAN OTC DRUG LABEL
Date: 20151006

ACTIVE INGREDIENTS: Hydrogen Peroxide 30 mg/1 mL
INACTIVE INGREDIENTS: Water; PHOSPHORIC ACID

maxim SOLUTION OF Hydrogen Peroxide

Active ingredient (by volume)

Hydrogen peroxide 3%

Purpose

first aid antiseptic/oral debriding agent

KEEP OUT OF REACH OF CHILDREN

Keep this and all drugs out of the reach of children. If swallowed, seek professional assistance or contact a Poison Control Center immediately. (1-800-222-1222)

INDICATIONS AND USAGE

Uses • first aid to help prevent the risk of infection in minor cuts, scrapes and burns • aids in the removal of phlegm, mucus, or other secretions associated with occasional sore mouth

Warnings

For external use only.

Do not use • in the eyes or apply over large areas of the body • longer than one week

Ask a doctor before use if you have • deep or puncture wounds, animal bites or serious burns.

Stop use and ask a doctor if • the condition persists or gets worse • sore mouth symptoms do not improve in 7 days • irritation, pain or redness persists or worsens • swelling, rash or fever develops

Directions

first aid antiseptic:

- clean affected area
- apply small amount of product on affected area 1-3 times a day
- may be covered with a sterile bandage
- if bandaged, let dry first

oral debriding agent (oral rinse):

- adults and children 2 years of age and over:
- mix with an equal amount of water
- swish around in the mouth over affected area for atleast 1 minute and then spit out
- use upto 4 times daily after meals and at bedtime or as directed by a dentist or doctor

- children under 12 years should be supervised in the use of this product
- children under 2 years of age; consult a dentist or doctor

Inactive ingredient purified water, Phosphoric acid as a stabilizer

Other information Keep tightly closed and in a dark place at a controlled room temperature. Do not shake bottle. Hold away from face when opening.

DO NOT USE IF IMPRINTED SEAL ON CAP IS BROKEN OR REMOVED.

3% Topical Solution USP

TOPICAL ANTI-INFECTIVE

- For treatment of minor cuts and abrasions.

Imported by:

OSTL INC. 5805, White Oak Ave Suite # 16065

Encino, CA 91416, USA

www.ostltrade.com

Made in India